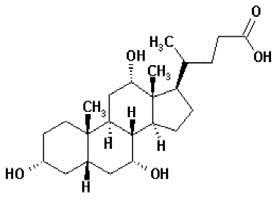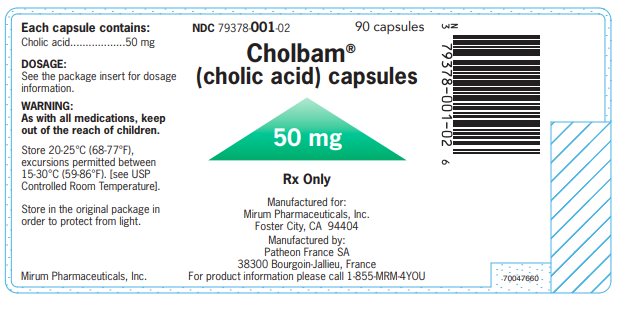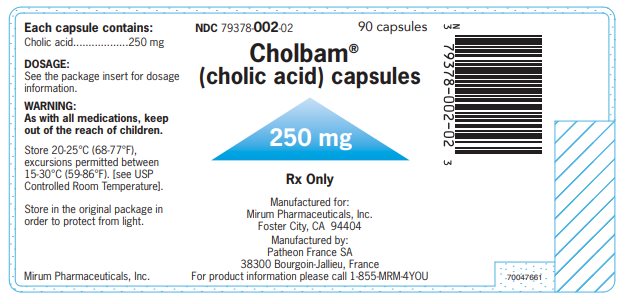 DRUG LABEL: CHOLBAM
NDC: 79378-001 | Form: CAPSULE
Manufacturer: Mirum Pharmaceuticals Inc.
Category: prescription | Type: HUMAN PRESCRIPTION DRUG LABEL
Date: 20260126

ACTIVE INGREDIENTS: CHOLIC ACID 50 mg/1 1
INACTIVE INGREDIENTS: MAGNESIUM STEARATE; MICROCRYSTALLINE CELLULOSE; CROSPOVIDONE, UNSPECIFIED; GELATIN, UNSPECIFIED; FERRIC OXIDE RED; TITANIUM DIOXIDE

HIGHLIGHTS OF PRESCRIBING INFORMATION

These highlights do not include all the information needed to use CHOLBAM® safely and effectively. See full prescribing information for CHOLBAM.
CHOLBAM (cholic acid) capsules, for oral use
Initial U.S. Approval: 2015

1 INDICATIONS AND USAGE

CHOLBAM is a bile acid indicated for:

- Treatment of bile acid synthesis disorders due to single enzyme defects (SEDs). (1.1)
- Adjunctive treatment of peroxisomal disorders (PDs) including Zellweger spectrum disorders in patients who exhibit manifestations of liver disease, steatorrhea or complications from decreased fat-soluble vitamin absorption. (1.2)

Limitations of use:

The safety and effectiveness of CHOLBAM on extrahepatic manifestations of bile acid synthesis disorders due to SEDs or PDs including Zellweger spectrum disorders have not been established. (1.3).

2 DOSAGE AND ADMINISTRATION

- The recommended dosage is 10 to 15 mg/kg once daily or in two divided doses, in pediatric patients and adults. See prescribing information for weight-based dosing tables. (2.1)
- The recommended dosage in patients with concomitant familial hypertriglyceridemia is 11 to 17 mg/kg once daily or in two divided doses and is adjusted based on clinical response. (2.1)
- Monitor AST, ALT, GGT, alkaline phosphatase, bilirubin and INR every month for the first 3 months, every 3 months for the next 9 months, every 6 months during the next three years and annually thereafter. Administer the lowest dose that effectively maintains liver function. (2.2)
- Discontinue CHOLBAM if liver function does not improve within 3 months of starting treatment, if complete biliary obstruction develops, or if there are persistent clinical or laboratory indicators of worsening liver function or cholestasis; continue to monitor liver function and consider restarting at a lower dose when parameters return to baseline. (2.2, 5.1)

Administration Instructions:

- Take with food. (2.3)
- Do not crush or chew the capsules. For patients unable to swallow the capsules, the capsules can be opened and the contents mixed with drink/food (2.3)

3 DOSAGE FORMS AND STRENGTHS

Capsules: 50 mg, 250 mg (3)

4 CONTRAINDICATIONS

None (4)

5 WARNINGS AND PRECAUTIONS

Exacerbation of Liver Impairment: Monitor liver function. Discontinue CHOLBAM if liver function worsens while on treatment. (5.1)

6 ADVERSE REACTIONS

Most common adverse reactions (≥1%) are diarrhea, reflux esophagitis, malaise, jaundice, skin lesion, nausea, abdominal pain, intestinal polyp, urinary tract infection, and peripheral neuropathy. (6.1)

To report SUSPECTED ADVERSE REACTIONS, contact Mirum Pharmaceuticals at 1-855-MRM-4YOU or FDA at 1-800-FDA-1088 or www.fda.gov/medwatch.

7 DRUG INTERACTIONS

- Bile Salt Efflux Pump (BSEP) Inhibitors (e.g., cyclosporine): Avoid concomitant use; if concomitant use is necessary, monitor serum transaminases and bilirubin (7.1)
- Bile Acid Resins and Aluminum-Based Antacids: Take CHOLBAM at least 1 hour before or 4 to 6 hours (or at as great an interval as possible) after a bile acid binding resin or aluminum-based antacids. (2.3, 7.1)

FULL PRESCRIBING INFORMATION

1 INDICATIONS AND USAGE

1.1 Bile Acid Synthesis Disorders Due to Single Enzyme Defects

CHOLBAM is indicated for the treatment of bile acid synthesis disorders due to single enzyme defects (SEDs).

1.2. Peroxisomal Disorders Including Zellweger Spectrum Disorders

CHOLBAM is indicated for adjunctive treatment of peroxisomal disorders (PDs) including Zellweger spectrum disorders in patients who exhibit manifestations of liver disease, steatorrhea or complications from decreased fat-soluble vitamin absorption.

1.3. Limitations of Use

The safety and effectiveness of CHOLBAM on extrahepatic manifestations of bile acid synthesis disorders due to SEDs or PDs including Zellweger spectrum disorders have not been established.

2 DOSAGE AND ADMINISTRATION

2.1. Dosage Regimen for Bile Acid Synthesis Disorders Due to SEDs and PDs Including Zellweger Spectrum Disorders

The recommended dosage of CHOLBAM is 10 to 15 mg/kg administered orally once daily or in two divided doses, in pediatric patients and adults.

Table 1 and Table 2 show the number of capsules that should be administered daily to approximate a dosage of 10 mg/kg/day and 15 mg/kg/day, respectively, using the available 50 mg and 250 mg capsules alone or in combination.

Table 1: Number of CHOLBAM Capsules Needed to Achieve a Recommended Dosage of 10 mg/kg/day
 | 10 mg/kg/day Dosage
Body Weight (kg) | Number of 50 mg capsules | Number of 250 mg capsules
4 to 6 | 1 | 0
7 to 10 | 2 | 0
11 to 15 | 3 | 0
16 to 20 | 4 | 0
21 to 25 | 0 | 1
26 to 30 | 1 | 1
31 to 35 | 2 | 1
36 to 40 | 3 | 1
41 to 45 | 4 | 1
46 to 50 | 0 | 2
51 to 55 | 1 | 2
56 to 60 | 2 | 2
61 to 65 | 3 | 2
66 to 70 | 4 | 2
71 to 75 | 0 | 3
76 to 80 | 1 | 3

Table 2: Number of CHOLBAM Capsules Needed to Achieve a Recommended Dosage of 15 mg/kg/day
 | 15 mg/kg/day Dosage
Body Weight (kg) | Number of 50 mg capsules | Number of 250 mg capsules
4 to 5 | 1 | 0
6 to 9 | 2 | 0
10 to 13 | 3 | 0
14 to 16 | 4 | 0
17 to 19 | 0 | 1
20 to 23 | 1 | 1
24 to 26 | 2 | 1
27 to 29 | 3 | 1
30 to 33 | 4 | 1
34 to 36 | 0 | 2
37 to 39 | 1 | 2
40 to 43 | 2 | 2
44 to 46 | 3 | 2
47 to 49 | 4 | 2
50 to 53 | 0 | 3
54 to 56 | 1 | 3
57 to 59 | 2 | 3
60 to 63 | 3 | 3
64 to 66 | 4 | 3
67 to 69 | 0 | 4
70 to 73 | 1 | 4
74 to 76 | 2 | 4
77 to 79 | 3 | 4
80 | 4 | 4

Patients with newly diagnosed, or a family history of, familial hypertriglyceridemia may have poor absorption of CHOLBAM from the intestine and require a 10% increase in the recommended dosage to account for losses due to malabsorption. The recommended dosage of CHOLBAM in patients with concomitant familial hypertriglyceridemia is 11 to 17 mg/kg orally once daily, or in two divided doses. Adequacy of the dosage regimen can be determined by monitoring the patient’s clinical response including steatorrhea and laboratory values of serum transaminases, bilirubin, and prothrombin time/international normalized ratio (PT/INR).

2.2. Treatment Monitoring

Treatment with CHOLBAM should be initiated and monitored by an experienced hepatologist or pediatric gastroenterologist.

Monitor serum aspartate aminotransferase (AST), serum alanine aminotransferase (ALT), serum gamma glutamyltransferase (GGT), alkaline phosphatase, bilirubin, and INR every month for the first 3 months, every 3 months for the next 9 months, every 6 months during the subsequent three years, and annually thereafter. Monitor more frequently during periods of rapid growth, concomitant disease, and pregnancy. Administer the lowest dose of CHOLBAM that effectively maintains liver function [see Warnings and Precautions (5.1)].

Discontinue treatment with CHOLBAM if liver function does not improve within 3 months of the start of treatment or if complete biliary obstruction develops.

Discontinue treatment with CHOLBAM at any time if there are persistent clinical or laboratory indicators of worsening liver function or cholestasis [see Warnings and Precautions (5.1)].

Concurrent elevations of serum GGT and serum ALT may indicate CHOLBAM overdose [see Overdosage (10)]. Continue to monitor laboratory parameters of liver function and consider restarting at a lower dose when parameters return to baseline.

Assessment of serum or urinary bile acid levels using mass spectrometry is used in the diagnosis of bile acid synthesis disorders due to SEDs and PDs including Zellweger spectrum disorders. The utility of bile acid measurements in monitoring the clinical course of patients and in decisions regarding dose adjustment has not been demonstrated.

2.3 Administration Instructions

- Take CHOLBAM with food.
- Take CHOLBAM at least 1 hour before or 4 to 6 hours (or at as great an interval as possible) after a bile acid binding resin or aluminum-based antacid.
- Do not crush or chew the capsules.
- For patients unable to swallow the capsules, open the capsules and mix the contents with infant formula or expressed breast milk (for younger children), or soft food such as mashed potatoes or apple puree (for older children and adults) in order to mask any unpleasant taste:
  1. Hold the capsule over the prepared liquid/food, gently twist open, and allow the contents to fall into the liquid/food.
  2. Mix the entire capsule contents with one or two tablespoons (15 mL to 30 mL) of infant formula, expressed breast milk, or soft food such as mashed potatoes or apple puree.
  3. Stir for 30 seconds.
  4. The capsule contents will remain as fine granules in the milk or food and will not dissolve.
  5. Administer the mixture immediately.

3 DOSAGE FORMS AND STRENGTHS

CHOLBAM is available in two capsule strengths:

- 50 mg capsule: Size number 2 Swedish orange capsule with cap imprinted with “50mg” and body imprinted with “ASK001”. The capsules contain a white to off-white powder.
- 250 mg capsule: Size number 0 white capsule with a cap imprinted with “250mg” and body imprinted with “ASK002”. The capsules contain a white to off-white powder.

4 CONTRAINDICATIONS

None.

5 WARNINGS AND PRECAUTIONS

5.1 Exacerbation of Liver Impairment

In clinical trials, evidence of liver impairment was present before treatment with CHOLBAM in approximately 86% (44/51) of patients with bile acid synthesis disorders due to SEDs and in approximately 50% (14/28) of patients with PDs including Zellweger spectrum disorders. Five of the patients (3 SED and 2 PD) with liver impairment at baseline experienced worsening serum transaminases, elevated bilirubin values, or worsening cholestasis on liver biopsy following treatment. Five additional patients (2 SED and 3 PD) who did not have baseline cholestasis experienced exacerbation of their liver disease while on treatment. In patients with cirrhosis, cases of severe hepatotoxicity have also been observed following postmarket use of CHOLBAM. Exacerbation of liver impairment by CHOLBAM in these patients cannot be ruled out.

Six patients with SEDs underwent liver transplant, including four patients diagnosed with AKR1D1 deficiency, one with 3β-HSD deficiency, and one with CYP7A1 deficiency.

Concurrent elevations of serum GGT and ALT may indicate CHOLBAM overdose [see Dosage and Administration (2.2) and Overdosage (10)].

Monitor liver function and discontinue CHOLBAM in patients who develop worsening of liver function while on treatment. Discontinue treatment with CHOLBAM at any time if there are clinical or laboratory indicators of worsening liver function or cholestasis [see Dosage and Administration (2.2)].

6 ADVERSE REACTIONS

The following clinically significant adverse reaction is described elsewhere in the labeling:

- Exacerbation of Liver Impairment [see Warnings and Precautions (5.1)]

6.1 Clinical Trials Experience

Because clinical trials are conducted under widely varying conditions, adverse reaction rates observed in the clinical trials of a drug cannot be directly compared to rates in the clinical trials of another drug and may not reflect the rates observed in practice.

Clinical safety experience with CHOLBAM consists of:

- Trial 1: a non-randomized, open-label, single-arm trial of 50 patients with bile acid synthesis disorders due to SEDs and 29 patients with PDs including Zellweger spectrum disorders. Safety data are available over the 18 years of the trial.
- Trial 2: an extension trial of 12 new patients (10 SED and 2 PD) along with 31 (21 SED and 10 PD) patients who rolled over from Trial 1. Safety data are available for 3 years and 11 months of treatment.

Adverse events were not collected systematically in either of these trials. Most patients received an oral dose of 10 to 15 mg/kg/day of CHOLBAM.

Deaths

In Trial 1, among the 50 patients with SEDs, 5 patients aged 1 year or less died, which included three patients originally diagnosed with AKR1D1 deficiency, one with 3β-HSD deficiency and one with CYP7A1 deficiency. The cause of death was attributed to progression of underlying liver disease in every patient.

Of 29 patients in Trial 1 with PDs including Zellweger spectrum disorders, 12 patients between the ages of 7 months and 2.5 years died. In the majority of these patients (8/12), the cause of death was attributed to progression of underlying liver disease or to a worsening of their primary illness.

Two additional patients in Trial 1 (1 SED and 1 PD) died who had been off study medication for more than one year with the cause of death most likely being a progression of underlying liver disease. Of the patients who died with disease progression, laboratory testing showed abnormal serum transaminases, bilirubin, or cholestasis on liver biopsy suggesting worsening of their underlying cholestasis.

In Trial 2, among the 31 patients with SED, two patients (1 new patient and 1 who rolled over from Trial 1) died. The cause of death in both cases was unrelated to their primary treatment or progression of their underlying liver disease.

Of the 12 patients with PD in Trial 2, four patients died between the ages of 4 and 8 years (1 new patient and 3 who rolled over from Trial 1). The cause of death in three of these patients was attributed to progression of underlying liver disease or to a worsening of their primary illness.

Worsening of Liver Impairment

Seven patients in Trial 1 (4 SED and 3 PD) and 3 patients in Trial 2 (1 SED and 2 PD) experienced worsening serum transaminases, elevated bilirubin values, or worsening cholestasis on liver biopsy during treatment [see Warnings and Precautions (5.1)].

Common Adverse Reactions

There were 12 adverse reactions reported across 9 patients in the trials, with diarrhea being the most common reaction in approximately 2% of the patient population. All other adverse reactions represented 1% of the patient population. The breakdown by trial follows:

Table 3: Most Common Adverse Reactions in Trials 1 and 2
Adverse Reactions | Trial 1 | Trial 2* | Overall n (%)
Diarrhea | 1 | 2* | 3 (2)
Reflux Esophagitis | 1 | 0 | 1 (1)
Malaise | 1 | 0 | 1 (1)
Jaundice | 1 | 0 | 1 (1)
Skin lesion | 1 | 0 | 1 (1)
Nausea | 0 | 1* | 1 (1)
Abdominal Pain | 0 | 1* | 1 (1)
Intestinal Polyp | 0 | 1* | 1 (1)
Urinary Tract Infection | 0 | 1* | 1 (1)
Peripheral Neuropathy | 0 | 1 | 1 (1)
*Adverse reactions that occurred in new patients

Only one of the reactions (peripheral neuropathy) resulted in discontinuation of medication for a patient in Trial 2. An additional five SED patients (3 from Trial 1 and 2 from Trial 2) and 1 PD patient (Trial 1) discontinued medication and withdrew from the study due to a worsening of their primary disease.

The development of symptomatic cholelithiasis requiring cholecystectomy has been reported in a single patient with 3β-HSD deficiency.

6.2. Postmarketing Experience

The following adverse reactions have been identified during post-approval use of CHOLBAM. Because these reactions are reported voluntarily from a population of uncertain size, it is not always possible to reliably estimate their relative frequency or to establish a causal relationship to CHOLBAM exposure:

- Gastrointestinal disorders: discomfort and distention, emesis, constipation
- General disorders and administrative site conditions: pyrexia/fever
- Skin and subcutaneous tissue disorders: rash

7 DRUG INTERACTIONS

7.1. Effects of Other Drugs on CHOLBAM

Drug interactions with CHOLBAM mainly relate to agents capable of interrupting the enterohepatic circulation of bile acids.

Inhibitors of Bile Acid Transporters

Avoid concomitant use of inhibitors of the bile salt efflux pump (BSEP) such as cyclosporine. Concomitant medications that inhibit canalicular membrane bile acid transporters such as the BSEP may exacerbate accumulation of conjugated bile salts in the liver and result in clinical symptoms. If concomitant use is deemed necessary, monitoring of serum transaminases and bilirubin is recommended.

Bile Acid Binding Resins

Bile acid binding resins such as cholestyramine, colestipol, or colesevelam adsorb and reduce bile acid absorption and may reduce the efficacy of CHOLBAM. Take CHOLBAM at least 1 hour before or 4 to 6 hours (or at as great an interval as possible) after a bile acid binding resin [see Dosage and Administration (2.3)].

Aluminum-Based Antacids

Aluminum-based antacids have been shown to adsorb bile acids in vitro and can reduce the availability of CHOLBAM. Take CHOLBAM at least 1 hour before or 4 to 6 hours (or at as great an interval as possible) after an aluminum-based antacid [see Dosage and Administration (2.3)].

8 USE IN SPECIFIC POPULATIONS

8.1 Pregnancy

Pregnancy Surveillance Program

There is a pregnancy surveillance program that monitors pregnancy outcomes in women exposed to CHOLBAM during pregnancy. Women who become pregnant during CHOLBAM treatment are encouraged to enroll. Patients or their health care provider should call Mirum Medical Information 1-855-676-4968.

Risk Summary

No studies in pregnant women or animal reproduction studies have been conducted with CHOLBAM. Limited published case reports discuss pregnancies in women taking cholic acid for 3β-HSD deficiency resulting in healthy infants. These reports may not adequately inform the presence or absence of drug-associated risk with the use of CHOLBAM during pregnancy.

The background risk of major birth defects and miscarriage for the indicated population is unknown. However, the background risk in the U.S. general population of major birth defects is 2-4% and of miscarriage is 15-20% of clinically recognized pregnancies.

8.2 Lactation

Risk Summary

Endogenous cholic acid is present in human milk. Clinical lactation studies have not been conducted to assess the presence of CHOLBAM in human milk, the effects of CHOLBAM on the breastfed infant, or the effects of CHOLBAM on milk production. There are no animal lactation data and no data from case reports available in the published literature. The developmental and health benefits of breastfeeding should be considered along with the mother’s clinical need for CHOLBAM and any potential adverse effects on the breastfed infant from CHOLBAM or from the underlying maternal condition.

8.4 Pediatric Use

The safety and effectiveness of CHOLBAM have been established in pediatric patients 3 weeks of age and older for the treatment of bile acid synthesis disorders due to SEDs and for adjunctive treatment of patients with PDs including Zellweger spectrum disorders who exhibit manifestations of liver disease, steatorrhea, or complications from decreased fat-soluble vitamin absorption [see Clinical Studies (14)].

8.5 Geriatric Use

Clinical studies of CHOLBAM did not include any patients aged 65 years and over. It is not known if elderly patients respond differently from younger patients.

8.6. Hepatic Impairment

Discontinue treatment with CHOLBAM if liver function does not improve within 3 months of the start of treatment.

Discontinue treatment with CHOLBAM at any time if there are clinical or laboratory indicators of worsening liver function or cholestasis [see Warnings and Precautions (5.1), Overdosage (10), and Nonclinical Toxicology (13.2)]. Continue to monitor laboratory parameters of liver function and consider restarting at a lower dose when the parameters return to baseline.

10 OVERDOSAGE

Concurrent elevations of serum GGT and ALT may indicate CHOLBAM overdose. If an overdose is suspected, discontinue CHOLBAM and treat symptoms. Continue to monitor laboratory parameters of liver function and consider restarting at a lower dose when the parameters return to baseline [see Dosage and Administration (2.2) and Warnings and Precautions (5.1)].

11 DESCRIPTION

Cholic acid is a bile acid. The chemical formula is C24H40O5, the molecular weight is 408.57 and the chemical structure is:

Cholic acid is a white to off-white powder. It is practically insoluble in water and in 0.1 M HCl at 20°C and is sparingly soluble in 0.1 M NaOH at 20°C. It is soluble in glacial acetic acid, alcohols, and acetone. A saturated solution in water at 20°C has a pH of 4.4.

CHOLBAM capsules contain 50 mg or 250 mg of cholic acid as the active ingredient in size 2 Swedish orange or size 0 white opaque gelatin capsules, respectively. Inactive ingredients in CHOLBAM include crospovidone, magnesium stearate, and silicified microcrystalline cellulose.

The size 2 capsule shells contain gelatin, red iron oxide and titanium dioxide, and the size 0 capsule shells contain gelatin and titanium dioxide. CHOLBAM is administered orally.

12 CLINICAL PHARMACOLOGY

12.1 Mechanism of Action

Cholic acid is a primary bile acid synthesized from cholesterol in the liver. In bile acid synthesis disorders due to SEDs in the biosynthetic pathway, and in PDs including Zellweger spectrum disorders, deficiency of primary bile acids leads to unregulated accumulation of intermediate bile acids and cholestasis. Bile acids facilitate fat digestion and absorption by forming mixed micelles and facilitate absorption of fat-soluble vitamins in the intestine.

Endogenous bile acids including cholic acid enhance bile flow and provide the physiologic feedback inhibition of bile acid synthesis. The mechanism of action of cholic acid has not been fully established; however, it is known that cholic acid and its conjugates are endogenous ligands of the nuclear receptor, farnesoid X receptor (FXR). FXR regulates enzymes and transporters that are involved in bile acid synthesis and in the enterohepatic circulation to maintain bile acid homeostasis under normal physiologic conditions.

12.3 Pharmacokinetics

Orally administered cholic acid is subject to the same metabolic pathway as endogenous cholic acid.

Cholic acid is absorbed by passive diffusion along the length of the gastrointestinal tract. Once absorbed, cholic acid enters into the body’s bile acid pool and undergoes enterohepatic circulation mainly in conjugated forms.

In the liver, cholic acid is conjugated with glycine or taurine by bile acid-CoA synthetase and bile acid-CoA:amino acid N-acyltransferase. Conjugated cholic acid is actively secreted into bile by the BSEP, and then released into the small intestines, along with other components of bile.

Conjugated cholic acid is mostly re-absorbed in the ileum mainly by the apical-sodium-dependent-bile acid transporter, passed back to the liver by transporters including sodium-taurocholate cotransporting polypeptide and organic anion transport protein and enters another cycle of enterohepatic circulation. Any conjugated cholic acid not absorbed in the ileum passes into the colon where deconjugation and 7-dehydroxylation are mediated by bacteria to form cholic acid and deoxycholic acid, which may be re-absorbed in the colon or excreted in the feces. The loss of cholic acid is compensated by de-novo synthesis of cholic acids from cholesterol to maintain the bile acid pool in healthy subjects.

13 NONCLINICAL TOXICOLOGY

13.1 Carcinogenesis, Mutagenesis, Impairment of Fertility

Carcinogenicity, genetic toxicology, and nonclinical fertility studies have not been performed with cholic acid.

13.2 Animal Toxicology and/or Pharmacology

In the PEX2-/- mouse model of peroxisomal disorders, feeding with a combination of cholic acid and ursodeoxycholic acid normalized C24 bile acid concentrations in bile to that of untreated control animals. Although growth was only mildly improved, there was near complete normalization of stool fat content, resolution of steatorrhea, and improved survival. Bile acid feeding reduced the number of cholestatic deposits in bile ducts and alleviated cholangitis but exacerbated the degree of hepatic steatosis and mitochondrial and cellular damage in the peroxisome-deficient livers of these animals.

14 CLINICAL STUDIES

14.1 Bile Acid Synthesis Disorders due to Single Enzyme Defects

The effectiveness of CHOLBAM at dosages of 10 to 15 mg/kg per day in patients with SEDs was assessed in:

- Trial 1: a non-randomized, open-label, single-arm trial in 50 patients over an 18‑year period
- Trial 2: an extension trial of 12 new patients along with 21 patients who rolled over from Trial 1 (n=33 total). Efficacy data are available for 21 months of treatment.
- A published case series of 15 patients with SEDs and 3 patients with PDs.

Enrollment criteria in Trials 1 and 2 were based on abnormal urinary bile acid by Fast Atom Bombardment ionization-Mass Spectrometry (FAB-MS).

Pre- and post-treatment liver biopsies were performed in a limited number of patients. Documentation of adherence to treatment, concomitant medications, and response to treatment were incomplete in Trial 1. Additional interventions in some patients included supplementation with fat-soluble vitamins, as dictated by the patient’s clinical signs and symptoms.

Trials 1 and 2

On average, patients were 4 years of age at the start of cholic acid treatment (range three weeks to 36 years). The majority of patients were treated for an average of 310 weeks (6 years). Patient ages at the end of treatment ranged from 19 to 36 years.

These trials were carried out over many years, and data are not available on all patients. Thirty-nine patients in Trial 1 and 5 new patients in Trial 2 received at least one dose of CHOLBAM and had sufficient data available to assess baseline liver function and effects of CHOLBAM treatment. A responder analysis was performed to determine the response to treatment with CHOLBAM.

Response to CHOLBAM treatment was assessed by the following laboratory criteria:

(1) ALT or AST values reduced to less than 50 U/L, or baseline levels reduced by 80%;
(2) total bilirubin values reduced to less than or equal to 1 mg/dL; and
(3) no evidence of cholestasis on liver biopsy;

and the following clinical criteria:

(1) body weight increased by 10% or stable at greater than the 50th percentile; and
(2) survival for greater than 3 years on treatment or alive at the end of Trial 2.

CHOLBAM responders were defined as patients who either:

(1) met at least two laboratory criteria and were alive at the last follow-up; or
(2) met at least one laboratory criteria, had increased body weight, and were alive at the last follow-up.

Overall, 28 of 44 patients (64%) were responders. The breakdown by defect type is as follows:

Table 4: Response to CHOLBAM Treatment by Type of Single Enzyme Defect
Single Enzyme Defect | Responders/Number Treated (%)
3β-HSD | 22/37 (59%)
AKR1D1 | 3/4 (75%)
CTX | 2/2 (100%)
AMACR | 1/1 (100%)
CYP7A1 | N/A*
Smith-Lemli-Opitz | N/A*
*N/A indicates no evaluable patients in the defect subgroup are represented.

Among SED responsive patients, 45% of the responders met the two clinical criteria plus 1 to 3 laboratory criteria and 55% met the weight criteria.

Only six patients had pre- and post-treatment liver biopsies in Trial 1. Where biopsies were available, pre-treatment biopsies showed varying degrees of inflammation, bridging fibrosis, and giant cell formation. Post-treatment biopsies generally showed reduced or absent inflammation and reduced or absent giant cell formation. Fibrosis remained but did not progress.

It is difficult to evaluate long term survival in patients with SEDs since there is little natural history survival data for comparison. Overall, 41 of 62 (67%) patients with SEDs survived greater than 3 years from trial entry. Thirteen of these 41 patients (32%) survived for 10 to 24 years on treatment.

Four patients in Trial 1 underwent liver transplant, including two patients diagnosed with AKR1D1 deficiency, one with 3β-HSD deficiency, and one with CYP7A1 deficiency and two patients in Trial 2, both with AKR1D1.

CHOLBAM’s effects on extrahepatic manifestations of SEDs, such as neurologic symptoms have not been established.

Case Series

A published report of a case series described 15 patients with SEDs; thirteen were diagnosed with 3β-HSD deficiency and two with AKR1D1 deficiency by mass spectrometry and gene sequencing. All patients were treated with cholic acid with a median duration of treatment of 12.4 years (range 5.6 to 15 years). Therapy started at a median age of 3.9 years (range 0.3 to 13.1 years). The mean dose at the start of cholic acid treatment was 13 mg/kg and the mean dose at last follow up was 6 mg/kg. Eight patients were initially treated with oral ursodeoxycholic acid prior to receiving a diagnosis of bile acid synthesis defect, after which they were switched to cholic acid. Initial signs and symptoms included jaundice, hepatosplenomegaly, steatorrhea, or symptoms related to deficiency of a fat-soluble vitamin (K, D or E).

Of the 8 patients who received ursodeoxycholic acid initially, the six with 3β-HSD deficiency demonstrated mild clinical improvement. Following treatment with cholic acid, all patients experienced resolution of their pre-existing jaundice and steatorrhea, and all but one experienced resolution of hepatosplenomegaly. Weight and height improved, and sexual maturation progressed normally in all patients. Liver biopsies were performed in 14 patients after at least 5 years of cholic acid treatment and all showed resolution of cholestasis. In one patient with 3β‑HSD deficiency, biliary bile acid analysis while on cholic acid therapy showed enrichment of the bile with cholic acid.

14.2 Peroxisomal Disorders Including Zellweger Spectrum Disorders

The effectiveness of CHOLBAM at a dosage of 10 to 15 mg/kg per day in patients with PDs including Zellweger spectrum disorders was assessed in patients in the same trials described in section 14.1.

- Trial 1 treated 29 patients with PDs over an 18‑year period.
- Trial 2 treated 2 new patients along with 10 patients who rolled over from Trial 1 (n=12 total). Efficacy data are available from Trial 2 for 21 months of treatment.
- Additional efficacy data were obtained from published case reports of 3 patients.

Enrollment criteria in Trials 1 and 2 were based on abnormal urinary bile acids analysis by FAB‑MS and a neurologic exam. Most patients received concomitant DHA (docosahexaenoic acid) and Vitamins A, D, E, and K. Documentation of adherence to treatment, concomitant medications, and response to treatment were incomplete during Trial 1.

Trials 1 and 2

The majority of patients (80%, 25/31) were less than 2 years of age at the start of CHOLBAM treatment (range 3 weeks to 10 years). The majority of patients were treated for an average of 254 weeks (4.8 years).

Sufficient data were available to assess baseline liver function and effects of CHOLBAM treatment in 23 patients in Trial 1 and in one new patient in Trial 2. A responder analysis was performed in the patients who had received at least one dose of CHOLBAM and had sufficient data available to assess baseline liver impairment.

Response to CHOLBAM treatment was assessed by the following laboratory criteria:

(1) ALT or AST values reduced to less than 50 U/L, or baseline levels reduced by 80%;
(2) total bilirubin values reduced to less than or equal to 1 mg/dL; and
(3) no evidence of cholestasis on liver biopsy;

and the following clinical criteria:

(1) body weight increased by 10% or stable at greater than the 50th percentile; and
(2) survival for greater than 3 years on treatment or alive at the end of Trial 2

CHOLBAM responders were defined as patients who either:

(1) met at least two laboratory criteria and were alive at the last follow-up; or
(2) met at least one laboratory criterion, had increased body weight and were alive at the last follow-up.

Overall, 11 of 24 patients (46%) were responders. The breakdown by disorder is as follows:

Table 5: Response to CHOLBAM Treatment by Type of Peroxisomal Disorders including Zellweger Spectrum Disorders
Peroxisomal Disorder | Responders/Number Treated (%)
Neonatal Adrenoleukodystrophy | 3/6 (50%)
Generalized Peroxisomal Disorder | 1/1 (100%)
Refsum Disease | 3/4 (75%)
Zellweger Syndrome | 3/8 (38%)
Peroxisomal Disorder, Type Unknown | 1/5 (20%)

Among responsive patients with PDs, 38% of the responders met the two clinical criteria plus 1 to 3 laboratory criteria and 63% met the weight criteria. There were no PD patients that underwent liver transplant.

No evidence of improvement in survival over that seen in historical controls could be demonstrated from the data presented. Overall, 13 of 31 patients (42%) survived greater than 3 years from the time of trial entry. Eight of these 13 patients (62%) survived 10 to 17 years on treatment.

Nine patients had both pre- and post-treatment liver biopsies. One patient showed improvement in histology, while the majority of patients remained unchanged. Two patients demonstrated worsening histology, which was consistent with a worsening of other liver laboratory parameters (bilirubin, serum transaminase values).

CHOLBAM’s effects on extrahepatic manifestations of PDs including Zellweger spectrum disorders, such as neurologic symptoms have not been established.

One patient, who did not have cholestasis on pre-treatment liver biopsy, developed cholestasis on treatment with CHOLBAM and subsequently died.

Case Reports

In case reports from the literature, a 6-month-old patient with Zellweger syndrome treated with a combination of cholic and chenodeoxycholic acids experienced normalization of serum transaminases and bilirubin, improvement in liver histology, reduced serum and urinary atypical bile acid intermediates, and improvement in steatorrhea and growth. Two patients with Zellweger syndrome treated with oral bile acids showed decreased serum transaminases.

16 HOW SUPPLIED/STORAGE AND HANDLING

50 mg Capsules

CHOLBAM capsules are available as two-piece gelatin capsules with a Swedish orange cap imprinted with “50mg” and Swedish orange body imprinted with “ASK001”. The capsules contain a white or off-white powder and are supplied in bottles of:

- 90 capsules (NDC 79378-001-02)

250 mg Capsules

CHOLBAM capsules are available as two-piece gelatin capsules with a white cap imprinted with “250mg” and white body imprinted with “ASK002”. The capsules contain a white or off-white powder and are supplied in bottles of:

- 90 capsules (NDC 79378-002-02)

Storage and Handling

Store at 20°C–25○C (68°F–77○F), excursions permitted between 15°C–30○C (59°F–86○F) [see USP Controlled Room Temperature].

17 PATIENT COUNSELING INFORMATION

Exacerbation of Liver Impairment [see Warnings and Precautions (5.1)]

- Advise patients that they will need to undergo laboratory testing periodically while on treatment to assess liver function.
- Advise patients that CHOLBAM may worsen liver impairment and that they should immediately report to their health care provider any symptoms associated with liver impairment (e.g., yellowing of the skin or the whites of the eye, dark or tea-colored urine, pain on the right side of stomach, bleeding or bruising occurs more easily than normal, or increased lethargy)

Administration [see Dosage and Administration (2.3)]

Advise patients:

- to take CHOLBAM with food.
- to take CHOLBAM at least one hour before or 4 to 6 hours after taking a bile acid binding resin or an aluminum-based antacid.
- not to crush or chew the capsules.
- for infants and children who cannot swallow capsules, the capsules can be opened and the contents mixed with either infant formula or expressed breast milk (for younger children), or soft food such as mashed potatoes or apple puree (for older children and adults) in order to mask any unpleasant taste:
  1. Hold the capsule over the prepared liquid/food, gently twist open, and allow the contents to fall into the liquid/food.
  2. Mix the entire capsule contents with one or two tablespoonfuls (15 mL or 30 mL) of infant formula, expressed breast milk, or soft food such as mashed potatoes or apple puree.
  3. Stir for 30 seconds.
  4. The capsule contents will remain as fine granules in the milk or food and will not dissolve.
  5. Administer the mixture immediately.

Pregnancy Surveillance Program [see Use in Specific Populations (8.1)]

Inform patients about the pregnancy surveillance program that monitors pregnancy outcomes in women exposed to CHOLBAM during pregnancy.

Manufactured by:
Patheon France S.A.S.
38300 Bourgoin-Jallieu, France

Manufactured for:
Mirum Pharmaceuticals, Inc.
Foster City, CA 94404
© 2026 Mirum Pharmaceuticals, Inc.
CHOLBAM® is a registered trademark of Mirum Pharmaceuticals, Inc.

LB00132v2

PACKAGE/LABEL PRINCIPAL DISPLAY PANEL

Each capsule contains:
Cholic acid..................50 mg

DOSAGE:
See the package insert for dosage
information.

WARNING:
As with all medications, keep
out of the reach of children.

Store 20-25°C (68-77°F),
excursions permitted between
15-30°C (59-86°F). [see USP
Controlled Room Temperature].

Store in the original package in
order to protect from light.

Mirum Pharmaceuticals, Inc.

NDC 79378-001-02 ; 90 capsules;

Cholbam® (cholic acid) capsules

(cholic acid) capsules; 50 mg; Rx Only

Manufactured for:
Mirum Pharmaceuticals, Inc.
Foster City, CA 94404

Manufactured by:
Patheon France SA
38300 Bourgoin-Jallieu, France
For product information please call 1-855-MRM-4YOU

PACKAGE/LABEL PRINCIPAL DISPLAY PANEL

Each capsule contains:
Cholic acid..................250 mg

DOSAGE:
See the package insert for dosage
information.

WARNING:
As with all medications, keep
out of the reach of children.

Store 20-25°C (68-77°F),
excursions permitted between
15-30°C (59-86°F). [see USP
Controlled Room Temperature].

Store in the original package in
order to protect from light.

Mirum Pharmaceuticals, Inc.

NDC 79378-002-02 ; 90 capsules;

Cholbam® (cholic acid) capsules

(cholic acid) capsules; 250 mg; Rx Only

Manufactured for:
Mirum Pharmaceuticals, Inc.
Foster City, CA 94404

Manufactured by:
Patheon France SA
38300 Bourgoin-Jallieu, France
For product information please call 1-855-MRM-4YOU